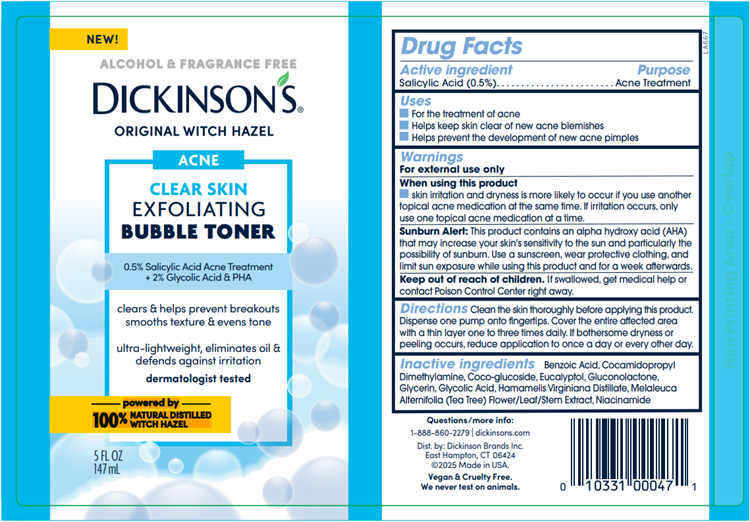 DRUG LABEL: Dickinsons Original Witch Hazel Exfoliating Bubble Toner
NDC: 52651-047 | Form: LIQUID
Manufacturer: Dickinson Brands Inc.
Category: otc | Type: HUMAN OTC DRUG LABEL
Date: 20250516

ACTIVE INGREDIENTS: SALICYLIC ACID 0.0039 g/1 mL
INACTIVE INGREDIENTS: BENZOIC ACID; COCAMIDOPROPYL DIMETHYLAMINE; COCO-GLUCOSIDE; EUCALYPTOL; GLUCONOLACTONE; GLYCERIN; GLYCOLIC ACID; HAMAMELIS VIRGINIANA TOP WATER; MELALEUCA ALTERNIFOLIA FLOWERING TOP; NIACINAMIDE

Dickinson's® Original Witch Hazel Exfoliating Bubble Toner

Drug Facts

Active ingredient

Salicylic Acid (0.5%)

Purpose

Acne Treatment

Uses

- For the treatment of acne
- Helps keep skin clear of new acne blemishes
- Helps prevent the development of new acne pimples

Warnings

For external use only

When using this product

- skin irritation and dryness is more likely to occur if you use another topical acne medication at the same time. If irritation occurs, only use one topical acne medication at a time.

Sunburn Alert

This product contains an alpha hydroxy acid (AHA) that may increase your skin's sensitivity to the sun and particularly the possibility of sunburn. Use a sunscreen, wear protective clothing, and limit sun exposure while using this product and for a week afterwards.

Keep out of reach of children. If swallowed, get medical help or contact Poison Control Center right away.

Directions

Clean the skin thoroughly before applying this product. Dispense one pump onto fingertips. Cover the entire affected area with a thin layer one to three times daily. If bothersome dryness or peeling occurs, reduce application to once a day or every other day.

Inactive ingredients

Benzoic Acid, Cocamidopropyl Dimethylamine, Coco-glucoside, Eucalyptol, Gluconolactone, Glycerin, Glycolic Acid, Hamamelis Virginiana Distillate, Melaleuca Alternifolia (Tea Tree) Flower/Leaf/Stem Extract, Niacinamide

Questions/more info:

1-888-860-2279 | dickinsons.com

Dist. by: Dickinson Brands Inc.
East Hampton, CT 06424

PRINCIPAL DISPLAY PANEL - 147 mL Bottle Label

NEW!

ALCOHOL & FRAGRANCE FREE

DICKINSON'S®

ORIGINAL WITCH HAZEL

ACNE

CLEAR SKIN
EXFOLIATING
BUBBLE TONER

0.5% Salicylic Acid Acne Treatment
+ 2% Glycolic Acid & PHA

clears & helps prevent breakouts
smooths texture & evens tone

ultra-lightweight, eliminates oil &
defends against irritation

dermatologist tested

powered by
100% NATURAL DISTILLED
WITCH HAZEL

5 FL OZ
147 mL